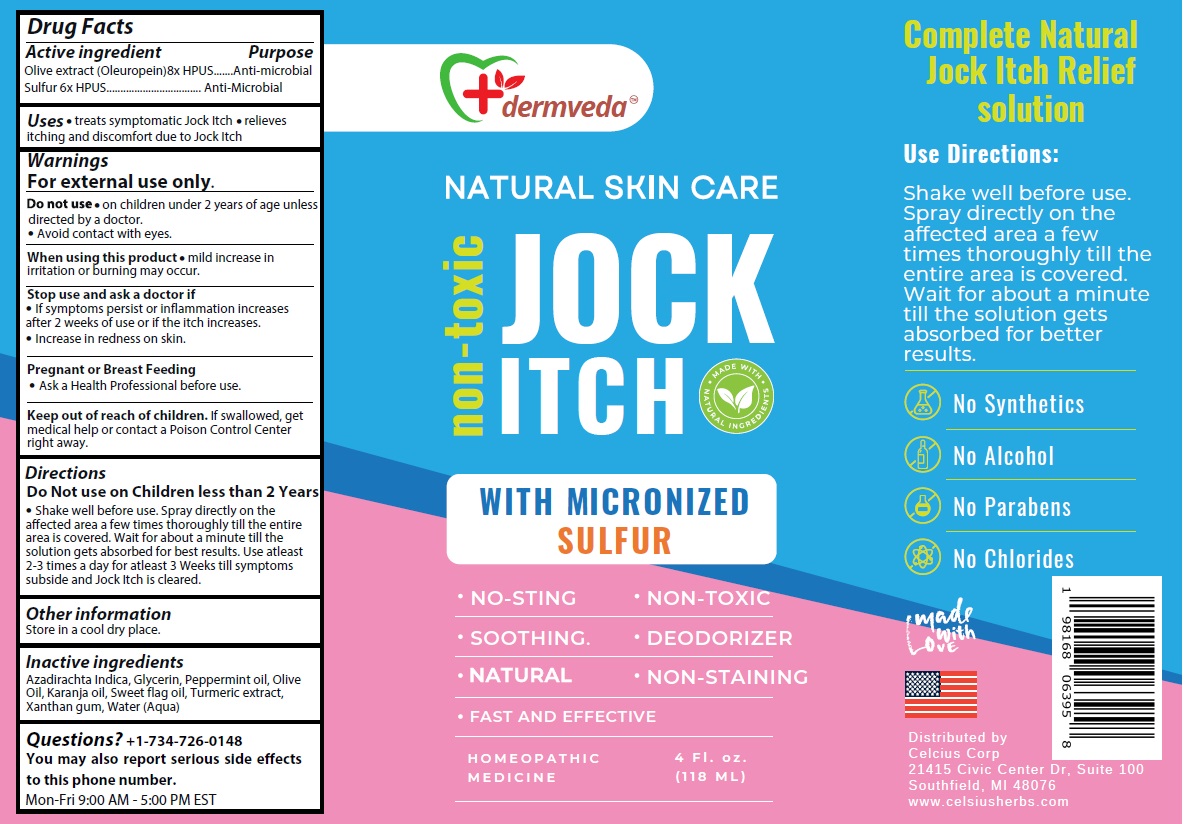 DRUG LABEL: dermveda JOCK ITCH
NDC: 83819-003 | Form: SPRAY
Manufacturer: Celcius Corp.
Category: homeopathic | Type: HUMAN OTC DRUG LABEL
Date: 20260206

ACTIVE INGREDIENTS: OLEA EUROPAEA (OLIVE) LEAF POWDER 8 [hp_X]/118 mL; SULFUR 6 [hp_X]/118 mL
INACTIVE INGREDIENTS: AZADIRACHTA INDICA SEED OIL; GLYCERIN; PEPPERMINT OIL; OLIVE OIL; KARUM SEED OIL; CALAMUS OIL; TURMERIC; XANTHAN GUM; WATER

dermveda™ JOCK ITCH

Active ingredient

Olive extract (Oleuropein) 8x HPUS
Sulfur 6x HPUS

Purpose

Anti-microbial

Uses

• treats symptomatic Jock Itch • relieves itching and discomfort due to Jock Itch

Warnings

For external use only.

Do not use • on children under 2 years of age unless directed by a doctor.
• Avoid contact with eyes.

When using this product • mild increase in irritation or burning may occur.

Stop use and ask a doctor if
• If symptoms persist or inflammation increases after 2 weeks of use or if the itch increases.
• Increase in redness on skin.

Pregnant or Breast Feeding
• Ask a Health Professional before use.

Keep out of reach of children. If swallowed, get medical help or contact a Poison Control Center right away.

Directions

Do Not use on Children less than 2 Years

• Shake well before use. Spray directly on the affected area a few times thoroughly till the entire area is covered. Wait for about a minute till the solution gets absorbed for best results. Use atleast 2-3 times a day for atleast 3 Weeks till symptoms subside and Jock Itch is cleared.

Other information

Store in a cool dry place.

Inactive ingredients

Azadirachta Indica, Glycerin, Peppermint oil, Olive Oil, Karanja oil, Sweet flag oil, Turmeric extract, Xanthan gum, Water (Aqua)

Questions?

+1-734-726-0148
You may also report serious side effects to this phone number.
Mon-Fri 9:00 AM - 5:00 PM EST

NATURAL SKIN CARE

MADE WITH NATURAL INGREDIENTS

WITH MICRONIZED SULFUR

• NO-STING • NON-TOXIC
• SOOTHING. • DEODORIZER
• NATURAL • NON-STAINING
• FAST AND EFFECTIVE

HOMEOPATHIC MEDICINE

Complete Natural Jock Itch Relief solution

No Synthetics
No Alcohol
No Parabens
No Chlorides

made with Love

Distributed by
Celcius Corp
21415 Civic Center Dr, Suite 100
Southfield, MI 48076
www.celsiusherbs.com